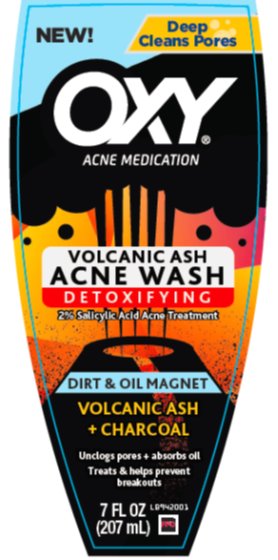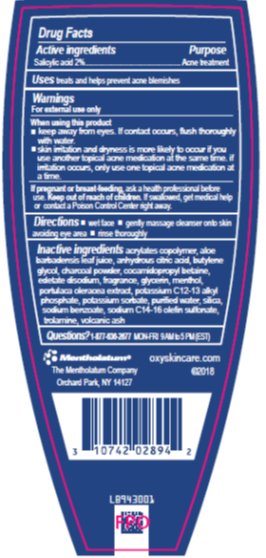 DRUG LABEL: OXY Volcanic Ash Acne Face Wash
NDC: 10742-8334 | Form: LIQUID
Manufacturer: The Mentholatum Company
Category: otc | Type: HUMAN OTC DRUG LABEL
Date: 20241217

ACTIVE INGREDIENTS: SALICYLIC ACID 20 mg/1 mL
INACTIVE INGREDIENTS: ALOE VERA LEAF; ANHYDROUS CITRIC ACID; BUTYLENE GLYCOL; ACTIVATED CHARCOAL; COCAMIDOPROPYL BETAINE; EDETATE DISODIUM; GLYCERIN; MENTHOL, UNSPECIFIED FORM; PURSLANE; POTASSIUM SORBATE; WATER; SILICON DIOXIDE; SODIUM BENZOATE; SODIUM C14-16 OLEFIN SULFONATE; TROLAMINE

Drug Facts - OXY Volcanic Ash Acne Face Wash

Active ingredient

Salicylic acid 2%

Purpose

Acne treatment

Uses

treats and helps prevent acne blemishes

Warnings

For external use only

When using this product

- keep away from eyes. If contact occurs, flush thoroughly with water.
- skin irritation and dryness is more likely to occur if you use another topical acne medication at the same time. If irritation occurs, only use one topical acne medication at a time.

If pregnant or breast-feeding,

ask a health professional before use

Keep out of reach of children.

If swallowed, get medical help or contact a Poison Control Center right away.

Directions

- wet face gently
- gently massage cleanser onto skin, avoiding eye area
- rinse thoroughly

Inactive ingredients

acrylates copolymer, aloe barbadensis leaf juice, anhydrous citric acid, butylene glycol, charcoal powder, cocamidopropyl betaine, edetate disodium, fragrance, glycerin, menthol, portulaca oleracea extract, potassium C12-13 alkyl phosphate, potassium sorbate, purified water, silica, sodium benzoate, sodium C14-16 olefin sulfonate, trolamine, volcanic ash

Questions?

1-877-636-2677 MON-FRI 9 AM to 5 PM (EST)